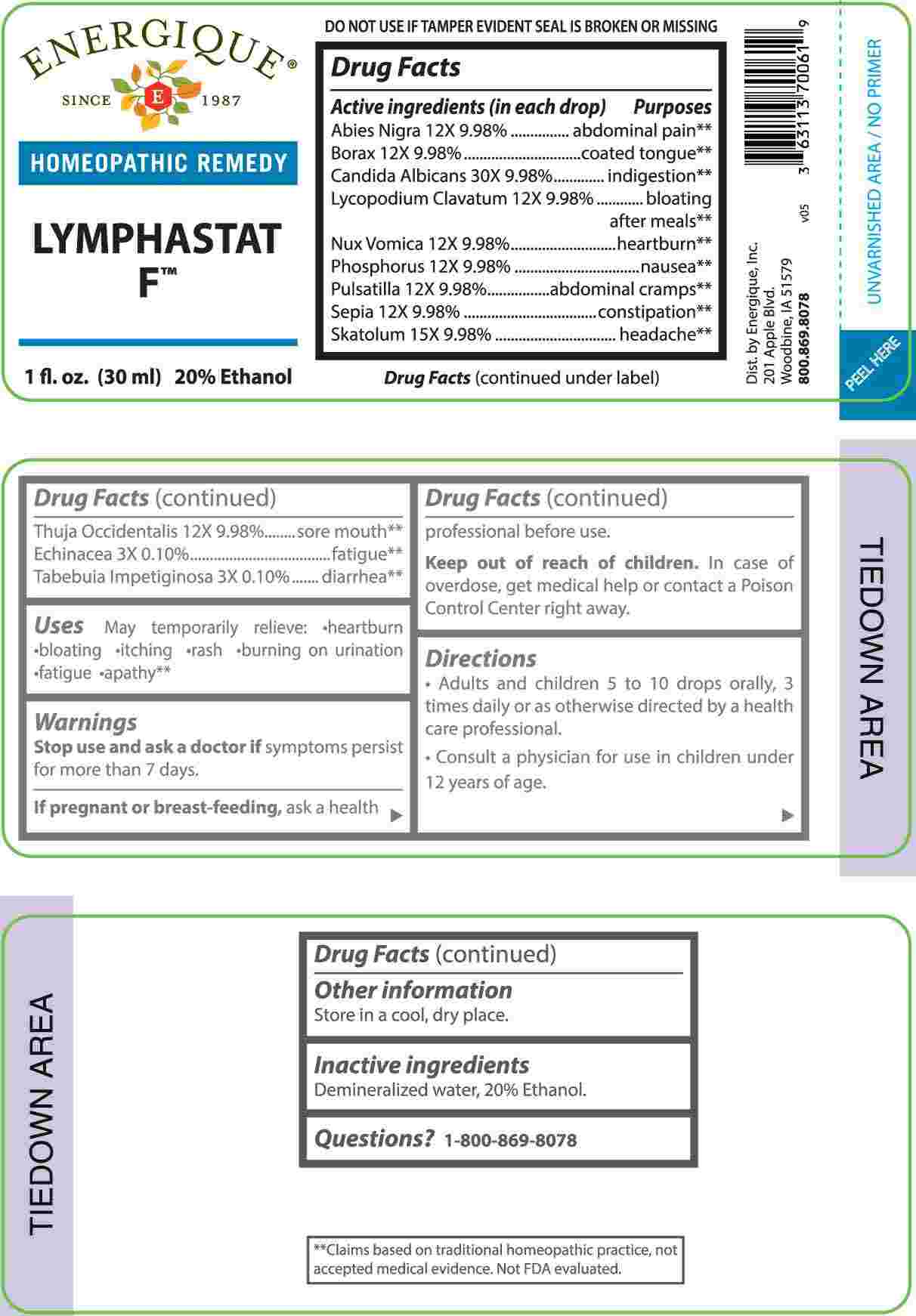 DRUG LABEL: Lymphastat F
NDC: 44911-0706 | Form: LIQUID
Manufacturer: Energique, Inc
Category: homeopathic | Type: HUMAN OTC DRUG LABEL
Date: 20240308

ACTIVE INGREDIENTS: ECHINACEA ANGUSTIFOLIA WHOLE 3 [hp_X]/1 mL; HANDROANTHUS IMPETIGINOSUS BARK 3 [hp_X]/1 mL; PICEA MARIANA RESIN 12 [hp_X]/1 mL; SODIUM BORATE 12 [hp_X]/1 mL; LYCOPODIUM CLAVATUM SPORE 12 [hp_X]/1 mL; STRYCHNOS NUX-VOMICA SEED 12 [hp_X]/1 mL; PHOSPHORUS 12 [hp_X]/1 mL; PULSATILLA VULGARIS WHOLE 12 [hp_X]/1 mL; SEPIA OFFICINALIS JUICE 12 [hp_X]/1 mL; THUJA OCCIDENTALIS LEAFY TWIG 12 [hp_X]/1 mL; SKATOLE 15 [hp_X]/1 mL; CANDIDA ALBICANS 30 [hp_X]/1 mL
INACTIVE INGREDIENTS: WATER; ALCOHOL

DRUG FACTS:

ACTIVE INGREDIENTS:

Abies Nigra 12X 9.98%, Borax 12X 9.98%, Candida Albicans 30X 9.98%, Lycopodium Clavatum 12X 9.98%, Nux Vomica 12X 9.98%, Phosphorus 12X 9.98%, Pulsatilla 12X 9.98%, Sepia 12X 9.98%, Skatolum 15X 9.98%, Thuja Occidentalis 12X 9.98%, Echinacea 3X 0.10%, Tabebuia Impetiginosa 3X 0.10%.

PURPOSE:

Abies Nigra – abdominal pain,** Borax – coated tongue,** Candida Albicans - indigestion,** Lycopodium Clavatum – bloating after meals,** Nux Vomica - heartburn,** Phosphorus - nausea,** Pulsatilla – abdominal cramps,** Sepia - constipation,** Skatolum - headache,** Thuja Occidentalis – sore mouth,** Echinacea - fatigue,** Tabebuia Impetiginosa – diarrhea**

USES:

May temporarily relieve: • heartburn • bloating • itching • rash • burning on urination • fatigue • apathy**

**Claims based on traditional homeopathic practice, not accepted medical evidence. Not FDA evaluated.

WARNINGS:

Stop use and ask a doctor if symptoms persist for more than 7 days.

If pregnant or breast-feeding, ask a health professional before use.

Keep out of reach of children. In case of overdose, get medical help or contact a Poison Control Center right away.

DO NOT USE IF TAMPER EVIDENT SEAL IS BROKEN OR MISSING

Store in a cool, dry place.

KEEP OUT OF REACH OF CHILDREN:

In case of overdose, get medical help or contact a Poison Control Center right away.

DIRECTIONS:

• Adults and children 5 to 10 drops orally, 3 times daily or as otherwise directed by a health care professional.

• Consult a physician for use in children under 12 years of age.

INACTIVE INGREDIENTS:

Demineralized water, 20% ethanol

QUESTIONS:

Dist. by Energique, Inc.

201 Apple Blvd.

Woodbine, IA 51579

800.869.8078

PACKAGE LABEL DISPLAY:

ENERGIQUE

SINCE 1987

HOMEOPATHIC REMEDY

LYMPHASTAT F

1 fl. oz. (30 ml)